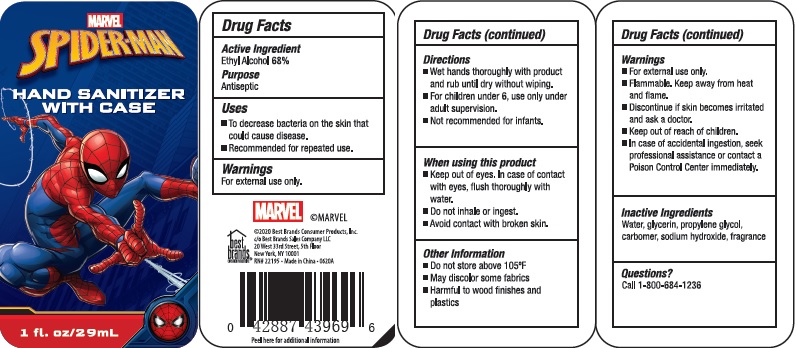 DRUG LABEL: MARVEL Spider-Man HAND SANITIZER With Case
NDC: 74274-022 | Form: GEL
Manufacturer: Huizhou Bliss Commodity Co., Ltd
Category: otc | Type: HUMAN OTC DRUG LABEL
Date: 20201007

ACTIVE INGREDIENTS: ALCOHOL 68 mL/100 mL
INACTIVE INGREDIENTS: WATER; PROPYLENE GLYCOL; GLYCERIN; SODIUM HYDROXIDE

Active ingredient

Ethyl Alcohol 68%

Purpose

Antiseptic

Use

- Decreases bacteria on the skin that could cause disease.
- Recommended for repeated use.

Warnings

- For external use only.
- Flammable.Keep away from heat or flame.
- Discontinue if skin becomes irritated and ask a doctor
- Keep out of reach of children.
- In case of accidental ingestion seek professional assistance or contact a Poison Control Center immediately.

When using this product

- Keep out of eyes. In case of contact with eyes, flush thoroughly with water.
- Do not inhale or ingest.
- Avoid contact with broken skin.

Keep out of reach of children.

If swallowed, get medical help or contact a Poison Control Center right away.

Directions

- Wet hands thoroughly with product and rub until dry without wiping.
- For children under 6, use only under adult supervison.
- Not recommended for infants.

Inactive ingredients

Water, glycerin, propyene glycol, carbomer, sodium hydroxide, fragrance

Questions？

Call 1-800-684-1236